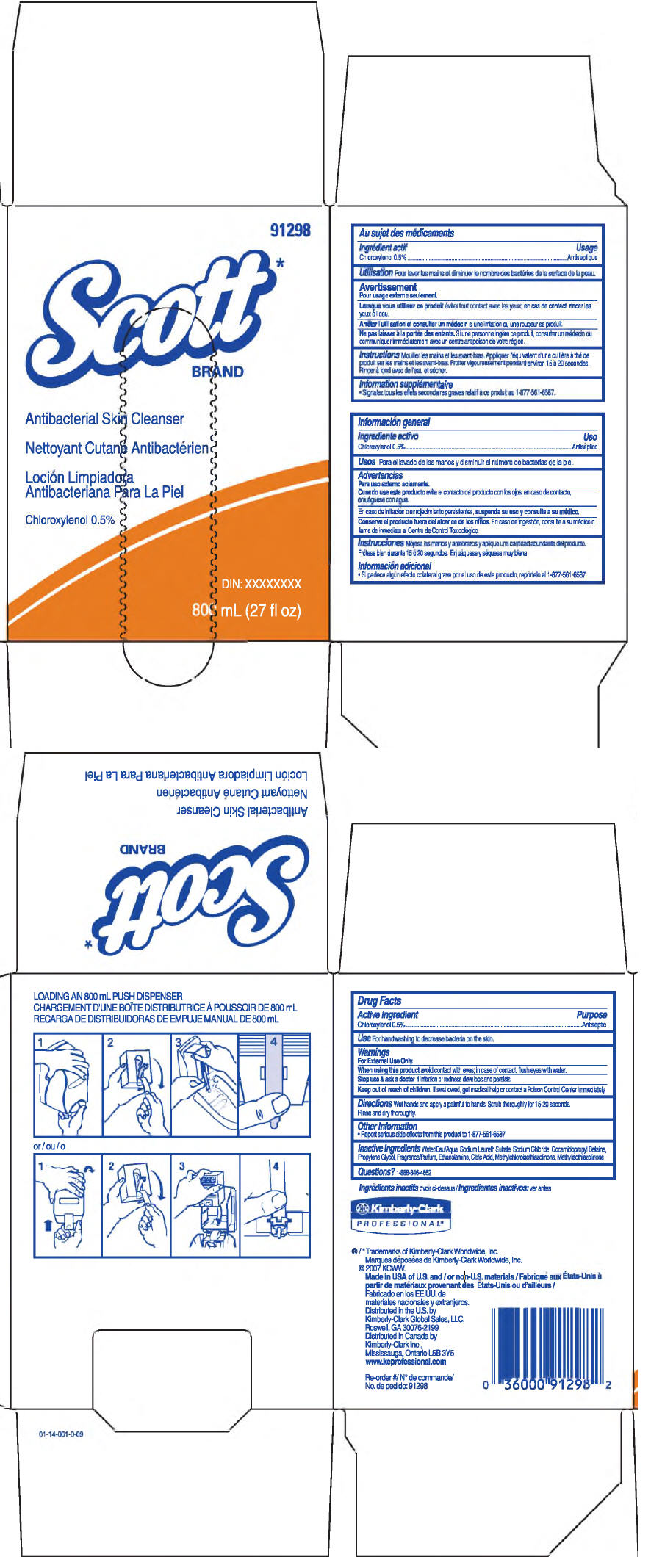 DRUG LABEL: Scott 
NDC: 55118-225 | Form: SOLUTION
Manufacturer: Kimberly-Clark Corporation
Category: otc | Type: HUMAN OTC DRUG LABEL
Date: 20141007

ACTIVE INGREDIENTS: Chloroxylenol 0.5 g/100 mL
INACTIVE INGREDIENTS: Water; Sodium Laureth-3 Sulfate; Sodium Chloride; Cocamidopropyl Betaine; Coco Diethanolamide; Propylene Glycol; Monoethanolamine; Citric Acid Monohydrate; Methylchloroisothiazolinone; Methylisothiazolinone

Scott Antibacterial Skin Cleanser

Drug Facts

Active Ingredient

Chloroxylenol 0.5%

Purpose

Antiseptic

Use

For handwashing to decrease bacteria on the skin.

Warnings

For External Use Only.

When using this product avoid contact with eyes; in case of contact, flush eyes with water.

STOP USE

Stop use & ask a doctor If irritation or redness develops and persists.

Keep out of reach of children. If swallowed, get medical help or contact a Poison Control Center immediately.

Directions

Wet hands and apply a palmful to hands. Scrub thoroughly for 15-20 seconds.

Rinse and dry thoroughly.

Other Information

- Report serious side effects from this product to 1-877-561-6587

Inactive Ingredients

Water, Sodium Laureth Sulfate, Sodium Chloride, Cocamidopropyl Betaine, Propylene Glycol, Fragrance, Ethanolamine, Citric Acid, Methylchloroisothiazolinone, Methylisothiazolinone

Questions?

1-888-346-4652

Distributed in the U.S. by
Kimberly-Clark Global Sales, LLC,
Roswell, GA 30076-2199

PRINCIPAL DISPLAY PANEL - 800 mL Container Label

91298

Scott*
BRAND

Antibacterial Skin Cleanser

Chloroxylenol 0.5%

DIN: XXXXXXXX

800 mL (27 fl oz)